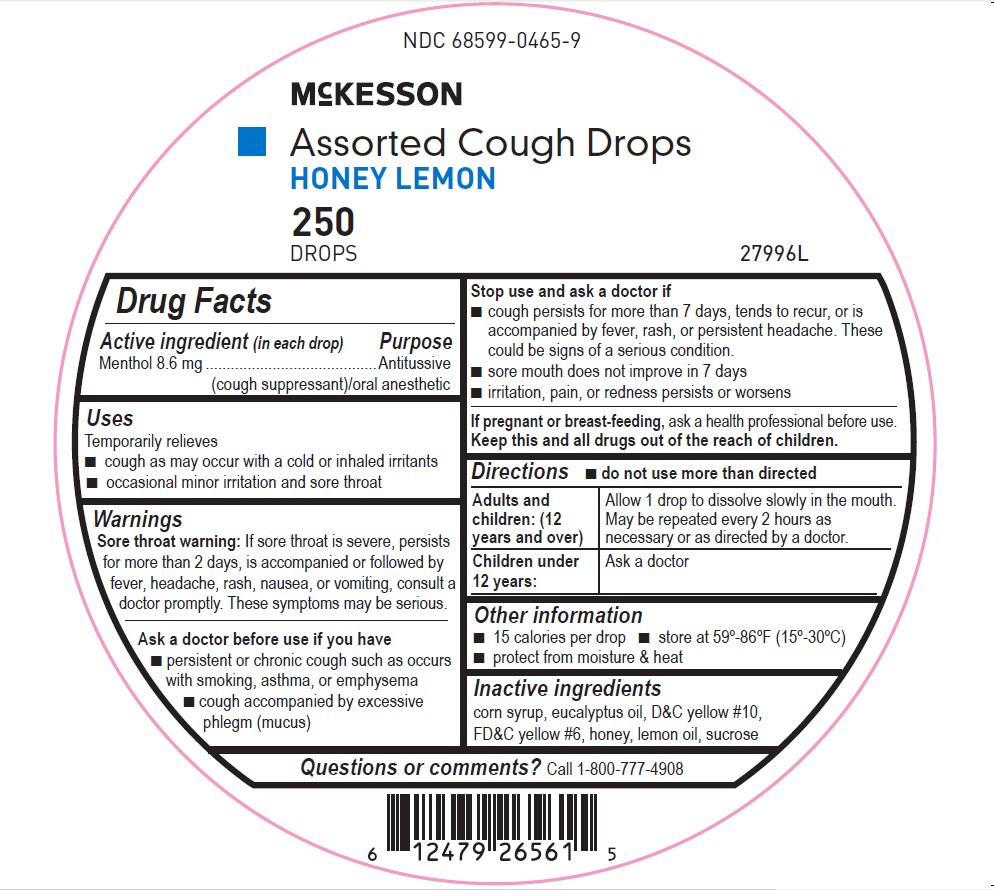 DRUG LABEL: Menthol
NDC: 68599-0465 | Form: LOZENGE
Manufacturer: McKesson
Category: otc | Type: HUMAN OTC DRUG LABEL
Date: 20241010

ACTIVE INGREDIENTS: MENTHOL, UNSPECIFIED FORM 0.86 g/1 g
INACTIVE INGREDIENTS: EUCALYPTUS OIL; LEMON OIL; SUCROSE; D&C YELLOW NO. 10; HONEY; FD&C YELLOW NO. 6; CORN SYRUP

Honey Lemon Cough Drops

Drug Facts

Active ingredient
Menthol 8.6 mg

Purpose
Antitussive (cough suppressant)/oral anesthetic

Uses
Temporarily relieves
■ cough as may occur with a cold or inhaled irritants
■ occasional minor irritation and sore throat

Warnings
Sore throat warning:If sore throat is severe, persists for more than 2 days, is accompanied or
followed by fever, headache, rash, nausea, or vomiting, consult a doctor promptly.

These symptoms may be serious.

Ask a doctor ifyou have
■ persistent or chronic cough such as occurs with smoking, asthma, or emphysema
■ cough accompanied by excessive phlegm (mucus)

Stop us e and ask a doctor if

- cough persists for more than 7 days, tends to recur, or is accompanied by fever, rash, or persistent

headache. These could be signs of a serious condition.

- sore mouth does not improve in 7 days
- irritation, pain or redness persists or worsens

If pregnant or breast-feeding, ask a health professional before use.

KEEP OUT OF REACH OF CHILDREN

Keep this and all drugs out of the reach of children.

Directions

- do not us e more than directed

Adults and children: (12 years and older)

- Allow 1 drop to dissolve slowly in the mouth. May be repeated every 2 hours as necessary or as directed by a doctor.

Children under 12 years:

- Do not give to children under 12 years of age.

Other information
■ 15 calories per drop
■ store at 59º-86ºF (15º-30ºC)
■ protect from moisture & heat

Inactive ingredients
corn syrup, D&C yellow # 10, eucalyptus oil, FD&C yellow # 6, honey, lemon oil, sucrose

Questions?Call 1-800-777-4908

PACKAGE LABEL

NDC# 68599-0465-9
McKesson
Cough Drops Assorted
Honey Lemon
250 per Jar
MFR# 27996L